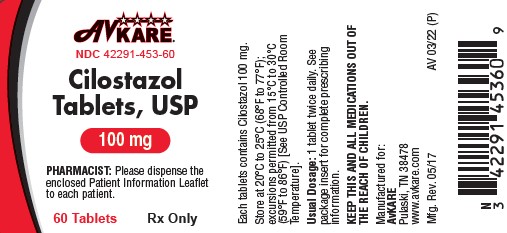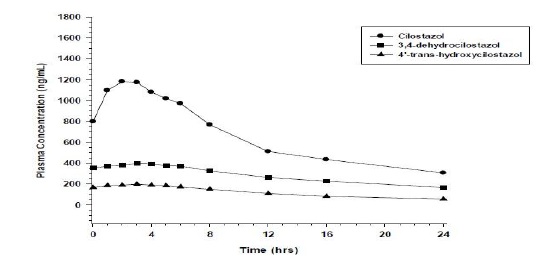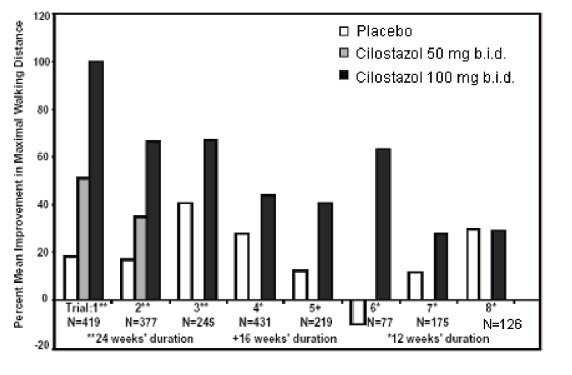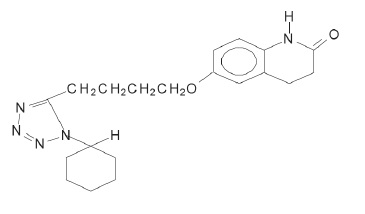 DRUG LABEL: cilostazol
NDC: 42291-453 | Form: TABLET
Manufacturer: AvKARE
Category: prescription | Type: HUMAN PRESCRIPTION DRUG LABEL
Date: 20260114

ACTIVE INGREDIENTS: CILOSTAZOL 100 mg/1 1
INACTIVE INGREDIENTS: STARCH, CORN; CROSCARMELLOSE SODIUM; MAGNESIUM STEARATE; SILICON DIOXIDE

HIGHLIGHTS OF PRESCRIBING INFORMATION

Cilostazol Tablets, USP
Rx only
These highlights do not include all the information needed to use CILOSTAZOL TABLETS safely and effectively. See full prescribing information for CILOSTAZOL TABLETS.
Initial U.S. Approval: 1999

WARNING: CONTRAINDICATED IN HEART FAILURE PATIENTS

See full prescribing information for complete boxed warning.

- Cilostazol tablets is contraindicated in patients with heart failure of any severity. Cilostazol and several of its metabolites are inhibitors of phosphodiesterase III. Several drugs with the pharmacologic effect have caused decreased survival compared to placebo patients with class III-IV heart failure. (4)

RECENT MAJOR CHANGES SECTION

Warnings and Precautions, Left Ventricular Outflow Obstruction (5.2) 05/2017

1 INDICATIONS AND USAGE

Cilostazol is a phosphodiesterase III inhibitor (PDE III inhibitor) indicated for the reduction of symptoms of intermittent claudication, as demonstrated by an increased walking distance (1)

2 DOSAGE AND ADMINISTRATION

- The recommended dosage of cilostazol is 100 mg twice daily taken at least half an hour before or two hours after breakfast and dinner (2.1)
- Reduce the dose to 50 mg twice daily when coadministered with CYP3A4 inhibitors such as ketoconazole, itraconazole, erythromycin, and diltiazem, or CYP2C19 inhibitors such as ticlopidine, fluconazole, and omeprazole (2.2)

3 DOSAGE FORMS AND STRENGTHS

- Tablets: 50 mg and 100 mg (3)

4 CONTRAINDICATIONS

- Heart failure of any severity (4)
- Hypersensitivity to cilostazol or any components of cilostazol tablets (4)

5 WARNINGS AND PRECAUTIONS

- Risks of tachycardia, palpitation, tachyarrhythmia or hypotension. Risks of exacerbations of angina pectoris or myocardial infarction in patients with a history of ischemic heart disease (5.2)
- Left ventricular outflow tract obstruction has been reported in patients with sigmoid shaped interventricular septum (5.1)
- Risks of thrombocytopenia or leukopenia progressing to agranulocytosis-monitor platelets and white blood cell counts (5.3)
- Avoid use in patients with hemostatic disorders or active pathologic bleeding (5.4)

6 ADVERSE REACTIONS

Most common adverse reactions greater than or equal to 2% and at least twice that for placebo in patients on 100 mg twice daily are headache, diarrhea, abnormal stools, and palpitation (6.1)

To report SUSPECTED ADVERSE REACTIONS, contact AvKARE at 1-855-361-3993; email drugsafety@avkare.com or FDA at 1-800-FDA-1088 or www.fda.gov/medwatch.

7 DRUG INTERACTIONS

- Strong and moderate CYP3A4 and CYP2C19 inhibitors: Increase exposure to cilostazol. Reduce cilostazol tablets dose (2.2, 7.1)

FULL PRESCRIBING INFORMATION

WARNING: CONTRAINDICATED IN HEART FAILURE PATIENTS

Cilostazol tablets are contraindicated in patients with heart failure of any severity. Cilostazol and several of its metabolites are inhibitors of phosphodiesterase III. Several drugs with this pharmacologic effect have caused decreased survival compared to placebo in patients with class III-IV heart failure [see Contraindications (4)] .

1 INDICATIONS AND USAGE

Cilostazol tablets are indicated for the reduction of symptoms of intermittent claudication, as demonstrated by an increased walking distance.

2 DOSAGE AND ADMINISTRATION

2.1 Recommended dosage

The recommended dosage of cilostazol is 100 mg twice daily taken at least half an hour before or two hours after breakfast and dinner.

Patients may respond as early as 2 to 4 weeks after the initiation of therapy, but treatment for up to 12 weeks may be needed before a beneficial effect is experienced. If symptoms are unimproved after 3 months, discontinue cilostazol.

2.2 Dose Reduction with CYP3A4 and CYP2C19 Inhibitors

Reduce dose to 50 mg twice daily when coadministered with strong or moderate inhibitors of CYP3A4 (e.g., ketoconazole, itraconazole, erythromycin, and diltiazem) or inhibitors of CYP2C19 (e.g., ticlopidine, fluconazole, and omeprazole) [see Drug Interactions (7.1)] .

3 DOSAGE FORMS AND STRENGTHS

Cilostazol tablets, USP 50 mg are white, round, flat-faced, bevelled-edge tablets, engraved "APO" on one side and "CIL" over "50" on the other side.

Cilostazol tablets, USP 100 mg tablets are white, round, flat-faced, bevelled-edge tablets, engraved "APO" on one side and "CIL" over "100" on the other side.

4 CONTRAINDICATIONS

Cilostazol is contraindicated in patients with:

- Heart failure of any severity: Cilostazol and several of its metabolites are inhibitors of phosphodiesterase III. Several drugs with this pharmacologic effect have caused decreased survival compared to placebo in patients with class III-IV heart failure.
- Hypersensitivity to cilostazol or any components of cilostazol tablets (e.g., anaphylaxis, angioedema)

5 WARNINGS AND PRECAUTIONS

5.1 Tachycardia

Cilostazol may induce tachycardia, palpitation, tachyarrhythmia or hypotension. The increase in heart rate associated with cilostazol is approximately 5 to 7 bpm. Patients with a history of ischemic heart disease may be at risk for exacerbations of angina pectoris or myocardial infarction.

5.2 Left Ventricular Outflow Tract Obstruction

Left ventricular outflow tract obstruction has been reported in patients with sigmoid shaped interventricular septum. Monitor patients for the development of a new systolic murmur or cardiac symptoms after starting cilostazol.

5.3 Hematologic Adverse Reactions

Cases of thrombocytopenia or leukopenia progressing to agranulocytosis when cilostazol was not immediately discontinued have been reported. Agranulocytosis is reversible on discontinuation of cilostazol. Monitor platelets and white blood cell counts periodically.

5.4 Hemostatic Disorders or Active Pathologic Bleeding

Cilostazol inhibits platelet aggregation in a reversible manner. Cilostazol has not been studied in patients with hemostatic disorders or active pathologic bleeding. Avoid use of cilostazol tablets in these patients.

6 ADVERSE REACTIONS

The following adverse reactions are discussed in greater detail in other sections of the labeling:

- Patients with Heart Failure [see Boxed Warning]
- Tachycardia [see Warnings and Precautions (5.1)]
- Left Ventricular Outflow Tract Obstruction [see Warnings and Precautions (5.2)]
- Hematologic Adverse Reactions [see Warnings and Precautions (5.3)]
- Hemostatic Disorders or Active Pathologic Bleeding [see Warnings and Precautions (5.4)]

6.1 Clinical Trials Experience

Because clinical trials are conducted under widely varying conditions, adverse reaction rates observed in the clinical trials of a drug cannot be directly compared to rates in the clinical trials of another drug and may not reflect the rates observed in practice.

Adverse reactions were assessed in eight placebo-controlled clinical trials involving patients exposed to either 50 or 100 mg twice daily cilostazol tablets (n=1301) or placebo (n=973), with a median treatment duration of 127 days for patients on cilostazol tablets and 134 days for patients on placebo.

The most frequent adverse reaction resulting in discontinuation of therapy in more than 3% of patients treated with cilostazol tablets was headache [50 mg twice daily (1.3%), 100 mg twice daily (3.5%) and placebo (0.3%)]. Other frequent causes of discontinuation included palpitation and diarrhea, both 1.1% for cilostazol tablets (all doses) versus 0.1% for placebo.

The most common adverse reactions, occurring in at least 2% of patients treated with cilostazol tablets 50 or 100 mg twice daily, are shown in Table 1.

Table 1: Most Common Adverse Reactions in Patients on cilostazol tablets 50 or 100 mg Twice Daily (Incidence at least 2% and Occurring More Frequently (≥ 2%) in the 100 mg Twice Daily Group than on Placebo)

Adverse Reactions | Placebo (N=973) | Cilostazol tablets 50 mg twice daily (N=303) | Cilostazol tablets 100 mg twice daily (N=998)
Headache | 14% | 27% | 34%
Diarrhea | 7% | 12% | 19%
Abnormal stools | 4% | 12% | 15%
Palpitation | 1% | 5% | 10%
Dizziness | 6% | 9% | 10%
Pharyngitis | 7% | 7% | 10%
Infection | 8% | 14% | 10%
Peripheral edema | 4% | 9% | 7%
Rhinitis | 5% | 12% | 7%
Dyspepsia | 4% | 6% | 6%
Abdominal pain | 3% | 4% | 5%
Tachycardia | 1% | 4% | 4%

Less frequent clinical significant adverse reactions (less than 2%) that were experienced by patients treated with cilostazol 50 mg twice daily or 100 mg twice daily in the eight controlled clinical trials and that occurred at a frequency in the 100 mg twice daily group greater than in the placebo group are listed below.

Body as a whole: fever, generalized edema, malaise

Cardiovascular: atrial fibrillation, heart failure, myocardial infarction, nodal arrhythmia, supraventricular tachycardia, ventricular extrasystoles, ventricular tachycardia

Digestive: anorexia, melena

Hematologic and Lymphatic: anemia

Metabolic and Nutritional: increased creatinine, hyperuricemia

Nervous: insomnia

Respiratory: epistaxis

Skin and Appendages: urticaria

Special Senses: conjunctivitis, retinal hemorrhage, tinnitus

Urogenital: urinary frequency

6.2 Postmarketing Experience

The following adverse reactions have been identified during post-approval use of cilostazol tablets. Because these reactions are reported voluntarily from a population of an unknown size, it is not always possible to reliably estimate their frequency or establish a causal relationship to drug exposure.

Blood and lymphatic system disorders:
Aplastic anemia, granulocytopenia, pancytopenia, bleeding tendency

Cardiac disorders:
Torsade de pointes and QTc prolongation in patients with cardiac disorders (e.g. complete atrioventricular block, heart failure; and bradyarrythmia), angina pectoris.

Gastrointestinal disorders:
Gastrointestinal hemorrhage, vomiting, flatulence, nausea

General disorders and administration site conditions:
Pain, chest pain, hot flushes

Hepatobiliary disorders:
Hepatic dysfunction/abnormal liver function tests, jaundice

Immune system disorders:
Anaphylaxis, angioedema, and hypersensitivity

Investigations:
Blood glucose increased, blood uric acid increased, increase in BUN (blood urea increased), blood pressure increase

Nervous system disorders:
Intracranial hemorrhage, cerebral hemorrhage, cerebrovascular accident, extradural hematoma and subdural hematoma

Renal and urinary disorders:
Hematuria

Respiratory, thoracic and mediastinal disorders:
Pulmonary hemorrhage, interstitial pneumonia

Skin and subcutaneous tissue disorders:
Hemorrhage subcutaneous, pruritus, skin eruptions including Stevens-Johnson syndrome, skin drug eruption (dermatitis medicamentosa), rash

Vascular disorders:
Subacute stent thrombosis, hypertension.

7 DRUG INTERACTIONS

7.1 Inhibitors of CYP3A4 or CYP2C19

Inhibitors of CYP3A4
Coadministration of strong (e.g., ketoconazole) and moderate (e.g., erythromycin, diltiazem and grapefruit juice) CYP3A4 inhibitors can increase exposure to cilostazol. Reduce cilostazol dose to 50 mg twice daily when coadministered with strong or moderate inhibitors of CYP3A4 [see Dosage and Administration (2.2) and Clinical Pharmacology (12.3)].

Inhibitors of CYP2C19
Coadministration with CYP2C19 inhibitors (e.g., omeprazole) increases systemic exposure of cilostazol active metabolites. Reduce cilostazol dose to 50 mg twice daily when coadministered with strong or moderate inhibitors of CYP2C19 [see Dosage and Administration (2.2) and Clinical Pharmacology (12.3)].

8 USE IN SPECIFIC POPULATIONS

8.1 Pregnancy

Teratogenic Effects
Pregnancy Category C.

Cilostazol has been shown to be teratogenic in rats at doses that are greater than 5-times the human MRHD on a body surface area basis. There are no adequate and well-controlled studies in pregnant women.

In a rat developmental toxicity study, oral administration of 1000 mg cilostazol/kg/day was associated with decreased fetal weights, and increased incidences of cardiovascular, renal, and skeletal anomalies (ventricular septal, aortic arch and subclavian artery abnormalities, renal pelvic dilation, 14th rib, and retarded ossification). At this dose, systemic exposure to unbound cilostazol in nonpregnant rats was about 5 times the exposure in humans given the MRHD. Increased incidences of ventricular septal defect and retarded ossification were also noted at 150 mg/kg/day (5 times the MRHD on a systemic exposure basis). In a rabbit developmental toxicity study, an increased incidence of retardation of ossification of the sternum was seen at doses as low as 150 mg/kg/day. In nonpregnant rabbits given 150 mg/kg/day, exposure to unbound cilostazol was considerably lower than that seen in humans given the MRHD, and exposure to 3,4-dehydro- cilostazol was barely detectable.

When cilostazol was administered to rats during late pregnancy and lactation, an increased incidence of stillborn and decreased birth weights of offspring was seen at doses of 150 mg/kg/day (5 times the MRHD on a systemic exposure basis).

8.3 Nursing Mothers

Transfer of cilostazol into milk has been reported in rats. Because many drugs are excreted in human milk and because of the potential for serious adverse reactions in nursing infants from cilostazol, discontinue nursing or discontinue cilostazol.

8.4 Pediatric Use

Safety and effectiveness of cilostazol in pediatric patients have not been established.

8.5 Geriatric Use

Of the total number of subjects (n = 2,274) in clinical studies of cilostazol, 56 percent were 65 years old and over, while 16 percent were 75 years old and over. No overall differences in safety or effectiveness were observed between these subjects and younger subjects, and other reported clinical experience has not identified differences in responses between the elderly and younger patients, but greater sensitivity of some older individuals cannot be excluded. Pharmacokinetic studies have not disclosed any age-related effects on the absorption, distribution, metabolism, and elimination of cilostazol and its metabolites.

8.6 Hepatic Impairment

No dose adjustment is required in patients with mild hepatic impairment. Patients with moderate or severe hepatic impairment have not been studied in clinical trials and dosing recommendations cannot be provided [see Clinical Pharmacology (12.3)].

8.7 Renal Impairment

No dose adjustment is required in patients with renal impairment. Patients on dialysis have not been studied, but, it is unlikely that cilostazol can be removed efficiently by dialysis because of its high protein binding (95 to 98%) [see Clinical Pharmacology (12.3)].

10 OVERDOSAGE

Information on acute overdosage with cilostazol in humans is limited. The signs and symptoms of an acute overdose can be anticipated to be those of excessive pharmacologic effect: severe headache, diarrhea, hypotension, tachycardia, and possibly cardiac arrhythmias. The patient should be carefully observed and given supportive treatment. Since cilostazol is highly protein-bound, it is unlikely that it can be efficiently removed by hemodialysis or peritoneal dialysis. The oral LD50 of cilostazol is greater than 5 g per kg in mice and rats and greater than 2 g per kg in dogs.

11 DESCRIPTION

Cilostazol is a quinolinone derivative that inhibits cellular phosphodiesterase (more specific for phosphodiesterase III). The empirical formula of cilostazol is C20H27N5O2, and its molecular weight is 369.47. Cilostazol is 6-[4-(1-cyclohexyl-1 H-tetrazol-5-yl) butoxy]-3,4-dihydro-2(1 H)-quinolinone, CAS-73963-72-1.

The structural formula is:

Cilostazol occurs as white to off-white crystals or as a crystalline powder that is slightly soluble in methanol and ethanol, and is practically insoluble in water, 0.1 N HCl, and 0.1 N NaOH.

Cilostazol tablets, USP for oral administration are available in 50 mg and 100 mg round, white tablets. Each tablet, in addition to the active ingredient, contains the following inactive ingredients: corn starch, croscarmellose sodium, magnesium stearate, and silicon dioxide.

Meets USP Dissolution Test 2

12 CLINICAL PHARMACOLOGY

12.1 Mechanism of Action

Cilostazol and several of its metabolites inhibit phosphodiesterase III activity and suppress cAMP degradation with a resultant increase in cAMP in platelets and blood vessels, leading to inhibition of platelet aggregation and vasodilation, respectively.

Cilostazol reversibly inhibits platelet aggregation induced by a variety of stimuli, including thrombin, ADP, collagen, arachidonic acid, epinephrine, and shear stress.

Cardiovascular effects:

Cilostazol affects both vascular beds and cardiovascular function. It produces heterogeneous dilation of vascular beds, with greater dilation in femoral beds than in vertebral, carotid or superior mesenteric arteries. Renal arteries were not responsive to the effects of cilostazol.

In dogs or cynomolgus monkeys, cilostazol increased heart rate, myocardial contractile force, and coronary blood flow as well as ventricular automaticity, as would be expected for a PDE III inhibitor. Left ventricular contractility was increased at doses required to inhibit platelet aggregation. A-V conduction was accelerated. In humans, heart rate increased in a dose-proportional manner by a mean of 5.1 and 7.4 beats per minute in patients treated with 50 and 100 mg twice daily, respectively.

12.2 Pharmacodynamics

Cilostazol’s effects on platelet aggregation were evaluated in both healthy subjects and in patients with stable symptoms of cerebral thrombosis, cerebral embolism, transient ischemic attack, or cerebral arteriosclerosis over a range of doses from 50 mg every day to 100 mg three times a day. Cilostazol significantly inhibited platelet aggregation in a dose-dependent manner. The effects were observed as early as 3 hours post-dose and lasted up to 12 hours following a single dose. Following chronic administration and withdrawal of cilostazol, the effects on platelet aggregation began to subside 48 hours after withdrawal and returned to baseline by 96 hours with no rebound effect. A cilostazol dosage of 100 mg twice daily consistently inhibited platelet aggregation induced with arachidonic acid, collagen and adenosine diphosphate (ADP). Bleeding time was not affected by cilostazol administration.

Effects on circulating plasma lipids have been examined in patients taking cilostazol. After 12 weeks, as compared to placebo, cilostazol 100 mg twice daily produced a reduction in triglycerides of 29.3 mg/dL (15%) and an increase in HDL-cholesterol of 4.0 mg/dL (≅ 10%).

Drug Interactions
Aspirin
Short-term (less than or equal to 4 days) coadministration of aspirin with cilostazol increased the inhibition of ADP- induced ex vivo platelet aggregation by 22% to 37% when compared to either aspirin or cilostazol alone. Short-term (less than or equal to 4 days) coadministration of aspirin with cilostazol increased the inhibition of arachidonic acid-induced ex vivo platelet aggregation by 20% compared to cilostazol alone and by 48% compared to aspirin alone. However, short- term coadministration of aspirin with cilostazol had no clinically significant impact on PT, aPTT, or bleeding time compared to aspirin alone. Effects of long-term coadministration in the general population are unknown.

In eight randomized, placebo-controlled, double-blind clinical trials, aspirin was coadministered with cilostazol to 201 patients. The most frequent doses and mean durations of aspirin therapy were 75 to 81 mg daily for 137 days (107 patients) and 325 mg daily for 54 days (85 patients). There was no apparent increase in frequency of hemorrhagic adverse effects in patients taking cilostazol and aspirin compared to patients taking placebo and equivalent doses of aspirin.

Warfarin
Cilostazol did not inhibit the pharmacologic effects (PT, aPTT, bleeding time, or platelet aggregation) of R- and S- warfarin after a single 25-mg dose of warfarin. The effect of concomitant multiple dosing of warfarin and cilostazol on the pharmacodynamics of both drugs is unknown.

12.3 Pharmacokinetics

Cilostazol is absorbed after oral administration. A high fat meal increases absorption, with an approximately 90% increase in Cmax and a 25% increase in AUC. Absolute bioavailability is not known. Cilostazol is extensively metabolized by hepatic cytochrome P-450 enzymes, mainly 3A4, and, to a lesser extent, 2C19, with metabolites largely excreted in urine. Two metabolites are active, with one metabolite appearing to account for at least 50% of the pharmacologic (PDE III inhibition) activity after administration of cilostazol.

Pharmacokinetics are approximately dose proportional. Cilostazol and its active metabolites have apparent elimination half-lives of about 11 to 13 hours. Cilostazol and its active metabolites accumulate about 2-fold with chronic administration and reach steady state blood levels within a few days. The pharmacokinetics of cilostazol and its two major active metabolites were similar in healthy subjects and patients with intermittent claudication due to peripheral arterial disease (PAD). Figure 1 shows the mean plasma concentration-time profile at steady state after multiple dosing of cilostazol 100 mg twice daily.

Figure 1: Mean Plasma Concentration-time Profile at Steady State after Multiple Dosing of cilostazol 100 mg Twice Daily

Distribution
Cilostazol is 95 to 98% protein bound, predominantly to albumin. The binding for 3,4-dehydro-cilostazol is 97.4% and for 4´-trans-hydroxy-cilostazol is 66%. Mild hepatic impairment did not affect protein binding. The free fraction of cilostazol was 27% higher in subjects with renal impairment than in healthy volunteers. The displacement of cilostazol from plasma proteins by erythromycin, quinidine, warfarin, and omeprazole was not clinically significant.

Metabolism
Cilostazol is eliminated predominantly by metabolism and subsequent urinary excretion of metabolites. Based on in vitro studies, the primary isoenzymes involved in cilostazol’s metabolism are CYP3A4 and, to a lesser extent, CYP2C19. The enzyme responsible for metabolism of 3,4-dehydro-cilostazol, the most active of the metabolites, is unknown.

Following oral administration of 100 mg radiolabeled cilostazol, 56% of the total analytes in plasma was cilostazol, 15% was 3,4-dehydro-cilostazol (4 to 7 times as active as cilostazol), and 4% was 4´-trans-hydroxy-cilostazol (20% as active as cilostazol).

Elimination
The primary route of elimination was via the urine (74%), with the remainder excreted in feces (20%). No measurable amount of unchanged cilostazol was excreted in the urine, and less than 2% of the dose was excreted as 3,4-dehydro- cilostazol. About 30% of the dose was excreted in urine as 4´-trans-hydroxy-cilostazol. The remainder was excreted as other metabolites, none of which exceeded 5%. There was no evidence of induction of hepatic microenzymes.

Special Populations
Age and Gender
The total and unbound oral clearances, adjusted for body weight, of cilostazol and its metabolites were not significantly different with respect to age (50 to 80 years) or gender.

Smokers
Population pharmacokinetic analysis suggests that smoking decreased cilostazol exposure by about 20%.

Hepatic Impairment
The pharmacokinetics of cilostazol and its metabolites were similar in subjects with mild hepatic disease as compared to healthy subjects.

Patients with moderate or severe hepatic impairment have not been studied.

Renal Impairment
The total pharmacologic activity of cilostazol and its metabolites was similar in subjects with mild to moderate renal impairment and in healthy subjects. Severe renal impairment increases metabolite levels and alters protein binding of the parent. The expected pharmacologic activity, however, based on plasma concentrations and relative PDE III inhibiting potency of parent drug and metabolites, appeared little changed. Patients on dialysis have not been studied, but, it is unlikely that cilostazol can be removed efficiently by dialysis because of its high protein binding (95 to 98%).

Drug Interactions
Cilostazol does not appear to inhibit CYP3A4.

Warfarin
Cilostazol did not inhibit the metabolism of R- and S-warfarin after a single 25-mg dose of warfarin.

Clopidogrel
Multiple doses of clopidogrel do not significantly increase steady state plasma concentrations of cilostazol.

Strong Inhibitors of CYP3A4
A priming dose of ketoconazole 400 mg (a strong inhibitor of CYP3A4), was given one day prior to coadministration of single doses of ketoconazole 400 mg and cilostazol 100 mg. This regimen increased cilostazol Cmax by 94% and AUC by 117%. Other strong inhibitors of CYP3A4, such as itraconazole, voriconazole, clarithromycin, ritonavir, saquinavir, and nefazodone would be expected to have a similar effect [see Dosage and Administration (2.2), Drug Interactions (7.1)].

Moderate Inhibitors of CYP3A4
Erythromycin and other macrolide antibiotics: Erythromycin is a moderately strong inhibitor of CYP3A4. Coadministration of erythromycin 500 mg every 8h with a single dose of cilostazol 100 mg increased cilostazol Cmax by 47% and AUC by 73%. Inhibition of cilostazol metabolism by erythromycin increased the AUC of 4´-trans-hydroxy- cilostazol by 141% [see Dosage and Administration (2.2)].

Diltiazem:
Diltiazem 180 mg decreased the clearance of cilostazol by ~30%. Cilostazol Cmax increased ~30% and AUC increased ~40% [see Dosage and Administration (2.2)].

Grapefruit Juice:
Grapefruit juice increased the Cmax of cilostazol by ~50%, but had no effect on AUC.

Inhibitors of CYP2C19
Omeprazole: Coadministration of omeprazole did not significantly affect the metabolism of cilostazol, but the systemic exposure to 3,4-dehydro-cilostazol was increased by 69%, probably the result of omeprazole’s potent inhibition of CYP2C19 [see Dosage and Administration (2.2)].

Quinidine
Concomitant administration of quinidine with a single dose of cilostazol 100 mg did not alter cilostazol pharmacokinetics.

Lovastatin
The concomitant administration of lovastatin with cilostazol decreases cilostazol Css, max and AUCτ by 15%. There is also a decrease, although nonsignificant, in cilostazol metabolite concentrations. Coadministration of cilostazol with lovastatin increases lovastatin and ß-hydroxylovastatin AUC approximately 70% and is not expected to be clinically significant.

13 NONCLINICAL TOXICOLOGY

13.1 Carcinogenesis, Mutagenesis, Impairment of Fertility

Dietary administration of cilostazol to male and female rats and mice for up to 104 weeks, at doses up to 500 mg/kg/day in rats and 1000 mg/kg/day in mice, revealed no evidence of carcinogenic potential. The maximum doses administered in both rat and mouse studies were, on a systemic exposure basis, less than the human exposure at the MRHD of the drug. Cilostazol tested negative in bacterial gene mutation, bacterial DNA repair, mammalian cell gene mutation, and mouse in vivo bone marrow chromosomal aberration assays. It was, however, associated with a significant increase in chromosomal aberrations in the in vitro Chinese Hamster Ovary Cell assay.

In female mice, cilostazol caused a reversible contraceptive effect at a dose (300 mg/kg) that was approximately 7.4-fold greater than the Maximum Recommended Human Dose (MRHD) on a body surface area basis. These findings have not been demonstrated in other animal species.

Cilostazol did not affect fertility or mating performance of male and female rats at doses as high as 1000 mg/kg/day. At this dose, systemic exposures (AUCs) to unbound cilostazol were less than 1.5 times in males, and about 5 times in females, the exposure in humans at the MRHD.

13.2 Animal Toxicology and/or Pharmacology

Repeated oral administration of cilostazol to dogs (30 or more mg/kg/day for 52 weeks, 150 or more mg/kg/day for 13 weeks, and 450 mg/kg/day for 2 weeks), produced cardiovascular lesions that included endocardial hemorrhage, hemosiderin deposition and fibrosis in the left ventricle, hemorrhage in the right atrial wall, hemorrhage and necrosis of the smooth muscle in the wall of the coronary artery, intimal thickening of the coronary artery, and coronary arteritis and periarteritis. At the lowest dose associated with cardiovascular lesions in the 52-week study, systemic exposure (AUC) to unbound cilostazol was less than that seen in humans at the maximum recommended human dose (MRHD) of 100 mg twice daily. Similar lesions have been reported in dogs following the administration of other positive inotropic agents (including PDE III inhibitors) and/or vasodilating agents. No cardiovascular lesions were seen in rats following 5 or 13 weeks of administration of cilostazol at doses up to 1500 mg/kg/day. At this dose, systemic exposures (AUCs) to unbound cilostazol were only about 1.5 and 5 times (male and female rats, respectively) the exposure seen in humans at the MRHD. Cardiovascular lesions were also not seen in rats following 52 weeks of administration of cilostazol at doses up to 150 mg/kg/day. At this dose, systemic exposures (AUCs) to unbound cilostazol were about 0.5 and 5 times (male and female rats, respectively) the exposure in humans at the MRHD. In female rats, cilostazol AUCs were similar at 150 and 1500 mg/kg/day. Cardiovascular lesions were also not observed in monkeys after oral administration of cilostazol for 13 weeks at doses up to 1800 mg/kg/day. While this dose of cilostazol produced pharmacologic effects in monkeys, plasma cilostazol levels were less than those seen in humans given the MRHD, and those seen in dogs given doses associated with cardiovascular lesions.

14 CLINICAL STUDIES

The ability of cilostazol to improve walking distance in patients with stable intermittent claudication was studied in eight, randomized, placebo-controlled, double-blind trials of 12 to 24 weeks’ duration involving 2,274 patients using dosages of 50 mg twice daily (n=303), 100 mg twice daily (n=998), and placebo (n=973). Efficacy was determined primarily by the change in maximal walking distance from baseline (compared to change on placebo) on one of several standardized exercise treadmill tests.

Compared to patients treated with placebo, patients treated with cilostazol 50 or 100 mg twice daily experienced statistically significant improvements in walking distances both for the distance before the onset of claudication pain and the distance before exercise-limiting symptoms supervened (maximal walking distance). The effect of cilostazol on walking distance was seen as early as the first on-therapy observation point of two or four weeks.

Figure 2 depicts the percent mean improvement in maximal walking distance, at study end for each of the eight studies.

Figure 2: Percent Mean Improvement in Maximal Walking Distance at Study End for the Eight Randomized, Double-Blind, Placebo-Controlled Clinical Trials

Across the eight clinical trials, the range of improvement in maximal walking distance in patients treated with cilostazol 100 mg twice daily, expressed as the change from baseline, was 28% to 100%.

The corresponding changes in the placebo group were –10% to 41%.

The Walking Impairment Questionnaire, which was administered in six of the eight clinical trials, assesses the impact of a therapeutic intervention on walking ability. In a pooled analysis of the six trials, patients treated with either cilostazol 100 mg twice daily or 50 mg twice daily reported improvements in their walking speed and walking distance as compared to placebo. Improvements in walking performance were seen in the various subpopulations evaluated, including those defined by gender, smoking status, diabetes mellitus, duration of peripheral artery disease, age, and concomitant use of beta blockers or calcium channel blockers. Cilostazol has not been studied in patients with rapidly progressing claudication or in patients with leg pain at rest, ischemic leg ulcers, or gangrene. Its long-term effects on limb preservation and hospitalization have not been evaluated.

A randomized, double-blind, placebo-controlled Phase IV study was conducted to assess the long-term effects of cilostazol, with respect to mortality and safety, in 1,439 patients with intermittent claudication and no heart failure. The trial stopped early due to enrollment difficulties and a lower than expected overall death rate. With respect to mortality, the observed 36-month Kaplan-Meier event rate for deaths on study drug with a median time on study drug of 18 months was 5.6% (95% CI of 2.8 to 8.4 %) on cilostazol and 6.8% (95% CI of 1.9 to 11.5 %) on placebo. These data appear to be sufficient to exclude a 75% increase in the risk of mortality on cilostazol, which was the a priori study hypothesis.

16 HOW SUPPLIED/STORAGE AND HANDLING

16.1 How supplied

Cilostazol tablets, USP are supplied as 50 mg and 100 mg tablets.

Cilostazol tablets, USP 50 mg are white, round, flat-faced, bevelled-edge tablets, engraved "APO" on one side and "CIL" over "50" on the other side.

Cilostazol tablets, USP 100 mg tablets are white, round, flat-faced, bevelled-edge tablets, engraved "APO" on one side and "CIL" over "100" on the other side.

Bottles of 60 NDC 42291-453-60

16.2 Storage and handling

Store cilostazol tablets at 25°C (77°F); excursions permitted from 15°C to 30°C (59°F to 86°F) [See USP Controlled Room Temperature].

17 PATIENT COUNSELING INFORMATION

Advise the patient to read the FDA-approved patient labeling (Patient Information)
Advise the patient:

- to take cilostazol tablets at least one-half hour before or two hours after food.
- to discuss with their doctor before taking any CYP3A4 or CYP2C19 inhibitors (e.g., omeprazole).
- that the beneficial effects of cilostazol tablets on the symptoms of intermittent claudication may not be immediate. Although the patient may experience benefit in 2 to 4 weeks after initiation of therapy, treatment for up to 12 weeks may be required before a beneficial effect is experienced. Discontinue cilostazol tablets if symptoms do not improve after 3 months.

Manufactured for:
AvKARE
Pulaski, TN 38478

Mfg. Rev. 05/17
AV 03/22 (P)

PATIENT INFORMATION

Cilostazol Tablets, USP
(sye loe' sta zol)
for oral use
50 mg and 100 mg

Read this Patient Information leaflet before you start taking cilostazol tablets and each time you get a refill. There may be new information. This information does not take the place of talking to your doctor about your medical condition or your treatment.

What is the most important information I should know about cilostazol tablets?

Cilostazol tablets can cause serious side effects:

- Cilostazol tablets stops a protein called phosphodiesterase III from working. Other similar drugs which affect this protein may cause death if you already have heart problems, called class 3 to 4 (III-IV) heart failure. Do not take cilostazol tablets if you have heart failure of any kind.

What are cilostazol tablets?

Cilostazol tablets is a prescription medicine used to reduce the symptoms of intermittent claudication and can increase your ability to walk further distances.

It is not known if cilostazol tablets is safe and effective for use in children.

How does cilostazol tablets work?

Improvement in symptoms may occur as soon as 2 weeks, but could take up to 12 weeks.

Who should not take cilostazol tablets?
Do not take cilostazol tablets if you:

- have heart problems (heart failure)
- are allergic to cilostazol or any of the ingredients in cilostazol tablets. See the end of this leaflet for a complete list of ingredients in cilostazol tablets.

Tell your doctor before taking this medicine if you have any of these conditions.

What should I tell my doctor before taking cilostazol tablets?
Before you take cilostazol tablets, tell your doctor if you:

- drink grapefruit juice. Taking cilostazol tablets and drinking grapefruit juice can increase the amount of cilostazol tablets causing side effects.
- have any other medical conditions.
- are pregnant or planning to become pregnant. It is not known if cilostazol tablets will harm your unborn baby.
- are breastfeeding or planning to breastfeed. It is not known if cilostazol tablets passes into your breast milk. You and your doctor should decide if you will take cilostazol tablets or breastfeed. You should not do both.

Tell your doctor about all the medicines you take, including prescription and over-the-counter medicines, vitamins and herbal supplements.

Ask your doctor for a list of these medicines if you are not sure. You can ask your pharmacist for a list of medicines that interact with cilostazol tablets. Know the medicines you take. Keep a list of them to show to your doctor and pharmacist when you get a new medicine.

How should I take cilostazol tablets?

- Take cilostazol tablets exactly as your doctor tells you to take it.
- Your doctor will tell you how much cilostazol tablets to take and when to take it.
- Your doctor may change your dose if needed.
- Take cilostazol tablets 30 minutes before you eat or 2 hours after you eat.

What are the possible side effects of cilostazol tablets?
Cilostazol tablets may cause serious side effects, including:

- heart problems. Taking cilostazol tablets may cause you to have heart problems, including a fast heart beat, palpitations, irregular heartbeat, and low blood pressure.
- See "What is the most important information I should know about cilostazol tablets?"
- severe allergic reactions (anaphylaxis, angioedema). Call your doctor or go to the nearest emergency room right away if you have any of the following signs or symptoms of a severe allergic reaction:
  - hives
  - swelling of your face, lips, mouth, or tongue
  - trouble breathing or wheezing
  - dizziness

- changes in your blood cell counts (thrombocytopenia or leukopenia). Your doctor should do blood tests to check your blood cell counts while you take cilostazol tablets.

The most common side effects of cilostazol tablets include:

- headache
- abnormal stools
- diarrhea

Tell your doctor if you have any side effect that bothers you or does not go away. These are not all the possible side effects of cilostazol tablets. For more information, ask your doctor or pharmacist.

Call your doctor for medical advice about side effects. You may report side effects to FDA at 1-800-FDA-1088.

How should I store cilostazol tablets?

Store cilostazol tablets at room temperature between 68°F to 77°F (20°C to 25°C).

Keep cilostazol tablets and all medicines out of the reach of children.

General information about the safe and effective use of cilostazol tablets.

Medicines are sometimes prescribed for purposes other than those listed in a Patient Information leaflet. Do not use cilostazol tablets for a condition for which it was not prescribed. Do not give cilostazol tablets to other people, even if they have the same symptoms that you have. It may harm them.

This Patient Information summarizes the most important information about cilostazol tablets. If you would like more information, talk with your doctor. You can ask your pharmacist or doctor for information about cilostazol tablets that is written for health professionals.

For more information, call Apotex Corp. at 1-855-361-3993.

What are the ingredients in cilostazol tablets?

Active ingredient: cilostazol
Inactive ingredients: corn starch, croscarmellose sodium, magnesium stearate, and silicon dioxide

This Patient Information has been approved by the U.S. Food and Drug Administration.

Manufactured for:
AvKARE
Pulaski, TN 38478

Mfg. Rev. 05/17
AV 03/22 (P)